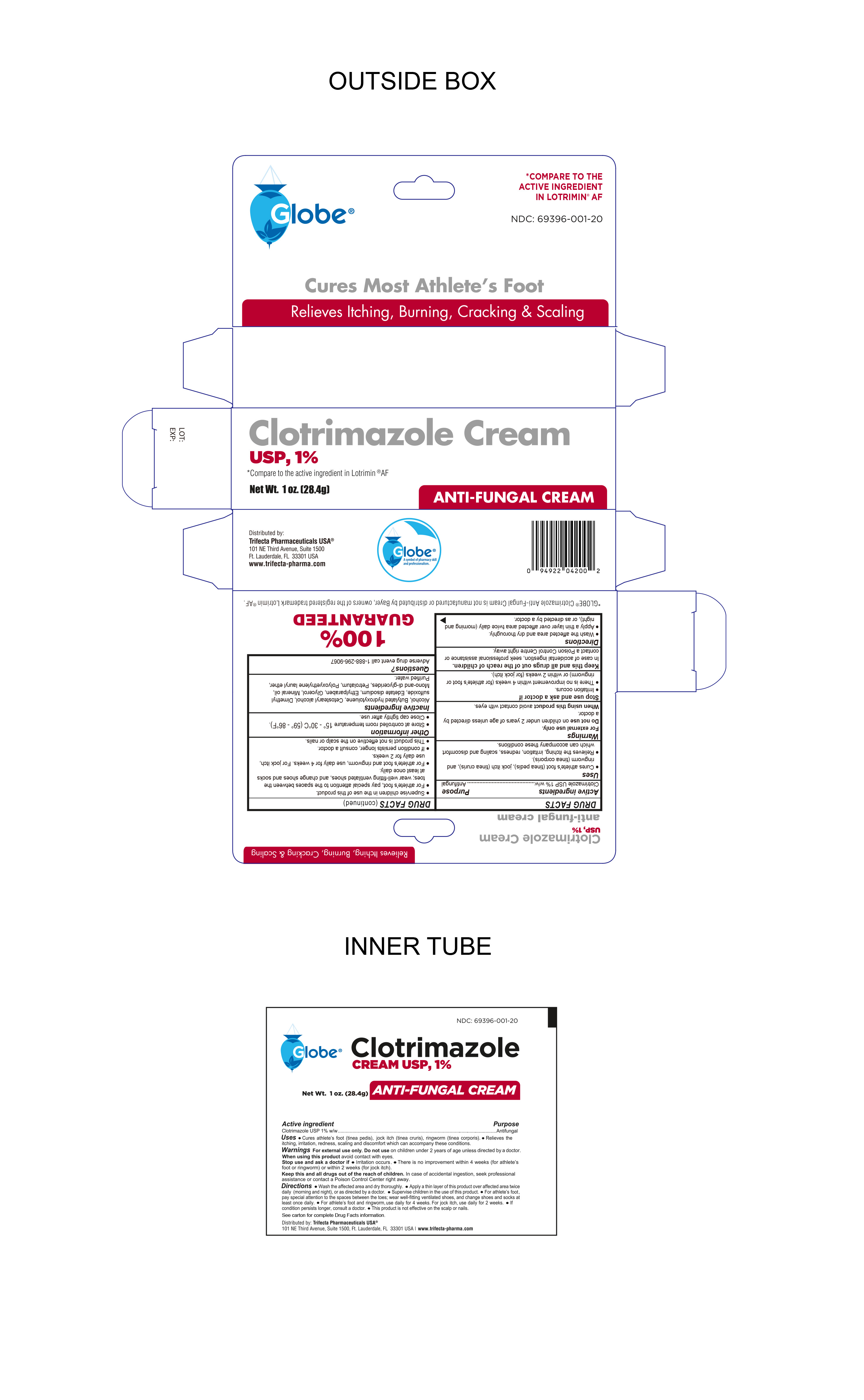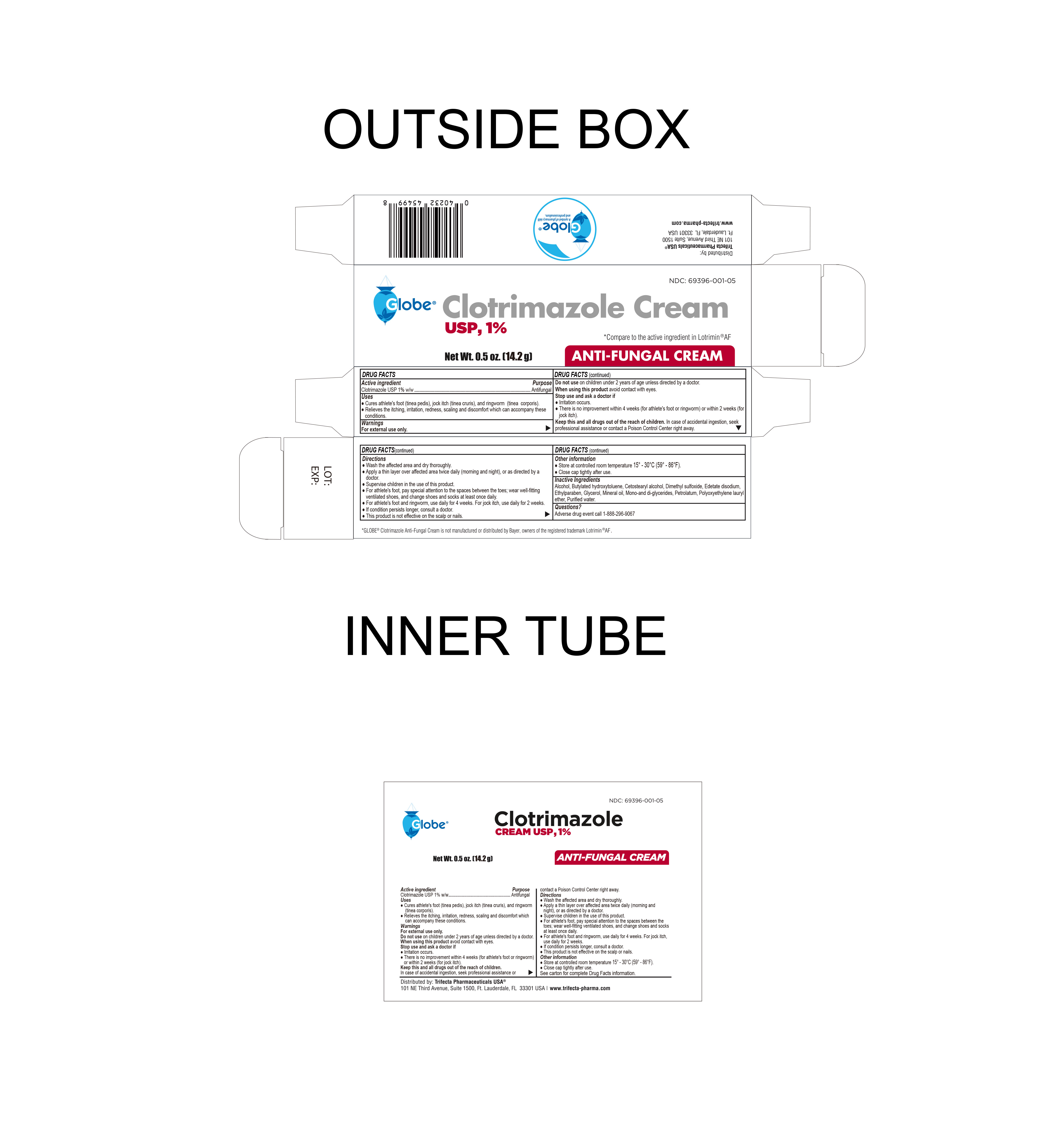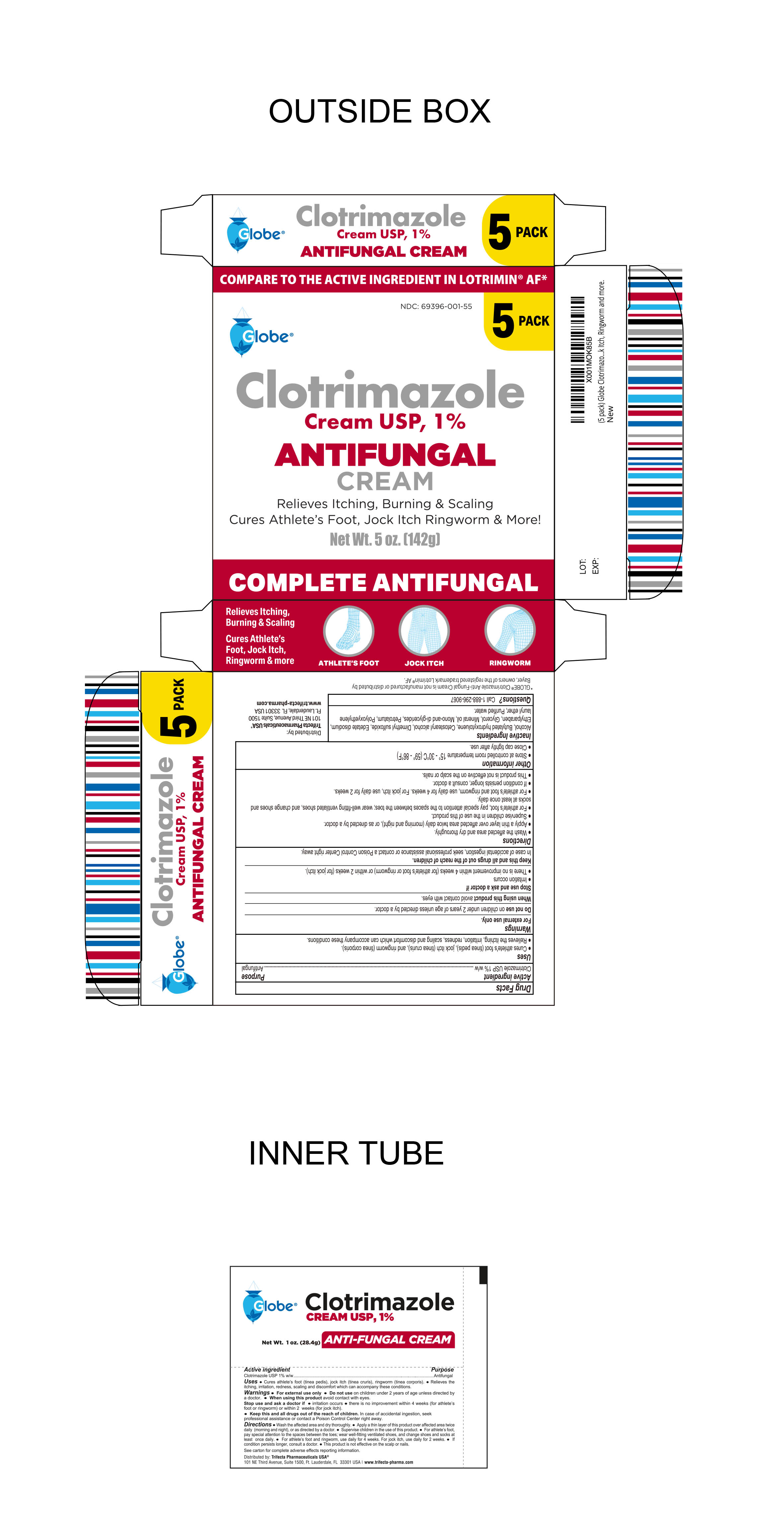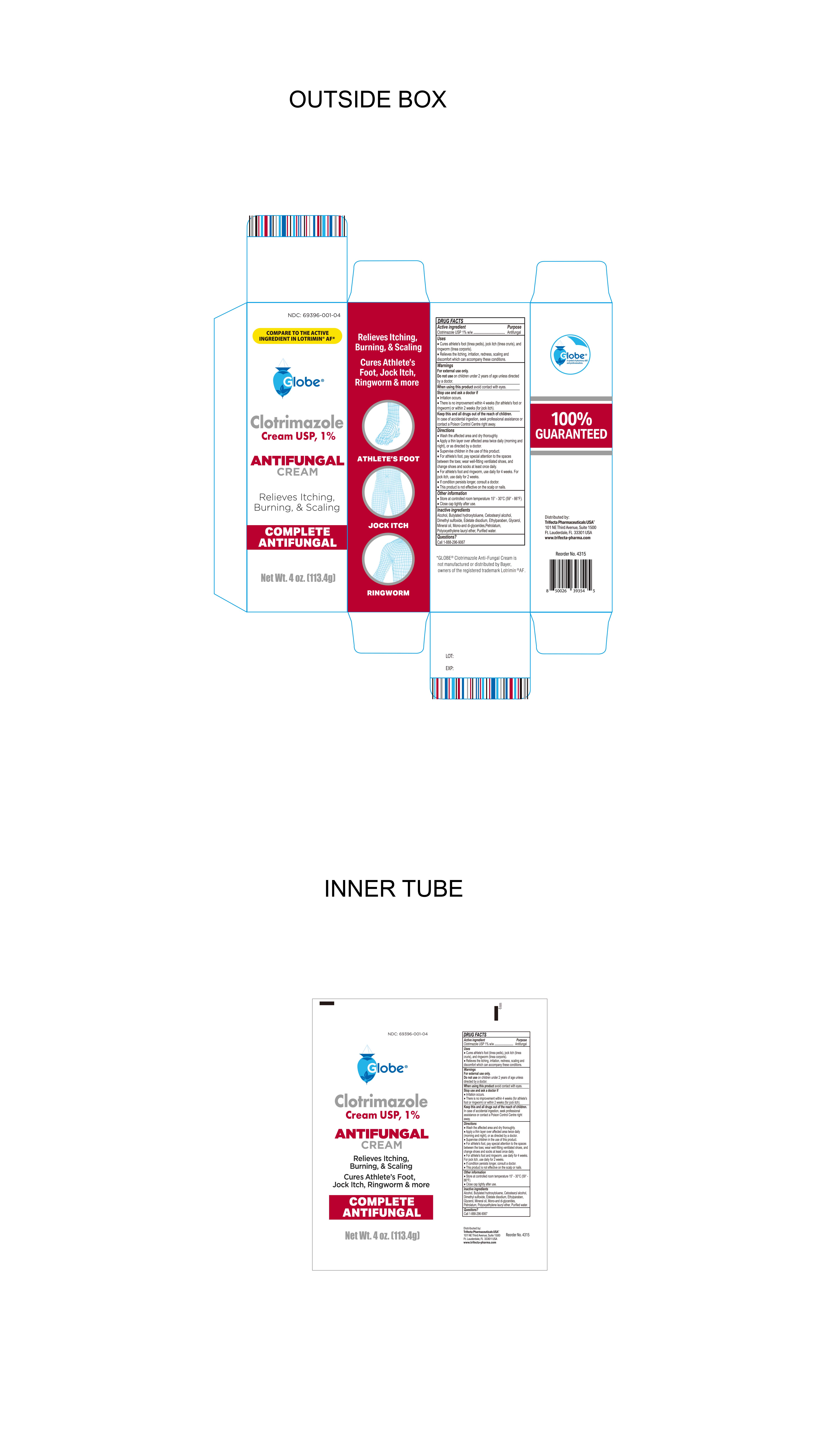 DRUG LABEL: Clotrimazole
NDC: 69396-001 | Form: CREAM
Manufacturer: TRIFECTA PHARMACEUTICALS USA LLC
Category: otc | Type: HUMAN OTC DRUG LABEL
Date: 20250823

ACTIVE INGREDIENTS: CLOTRIMAZOLE 1 g/100 g
INACTIVE INGREDIENTS: BUTYLATED HYDROXYTOLUENE; ALCOHOL; CETOSTEARYL ALCOHOL; MINERAL OIL; DIMETHYL SULFOXIDE; ETHYLPARABEN; GLYCERIN; LAURETH-23; PETROLATUM; WATER; EDETATE DISODIUM; GLYCERYL MONO AND DIPALMITOSTEARATE

Clotrimazole cream USP, 1%

Active ingredient

Clotrimazole USP 1% w/w

Purpose

Antifungal Cream

Uses

Cures athlete’s foot (tinea pedis), jock itch (tinea cruris), ringworm (tinea corporis). Relieves the itching, irritation, redness, scaling and discomfort which can accompany these conditions.

Warnings

For External use only.

KEEP OUT OF REACH OF CHILDREN

Keep this and all drugs out of the reach of children. In case of accidental ingestion, seek professional assistance or contact a Poison Control Center right away.

Do not use on children under 2 years of age unless direcgted by a doctor

When using this product avoid contact with eyes

Stop use and ask doctor if

- irritaion occurs
- There is no improvement within 4 weeks (for athlete's foot or ringworm) or within 2 weeks (for jock itch).

Keep this and all drugs out of the reach of children

In case of accidental ingestion, seek professional assistance or contact Poison Control Centre right away.

Directions

- Wash the affected area and dry thoroughly.

● Apply a thin layer of this product over affected area twice daily (morning and night), or as directed by a doctor.

● Supervise children in the use of this product.

● For athlete’s foot, pay special attention to the spaces between the toes; wear well-fitting ventilated shoes, and change shoes and socks at least once daily.

● For athlete’s foot and ringworm, use daily for 4 weeks. For jock itch, use daily for 2 weeks.

● If conditions persists longer, consult a doctor.

● This product is not effective on the scalp or nails.

Other Information

- store at controlled room temperature 15°-30°C (59°- 86°F)
- Close cap tightly after use.
- See carton for complete adverse effects reporting information.

Inactive Ingredients

Dimethyl Sulfoxide, Ethylparaben, Glycerin, Laureth-23, Mineral Oil, Petrolatum, Water, alcohol, Glyceryl mono and dipalmitostearate, Cetostearyl alcohol, edetate disodium, Butylated Hydroxytoluene.

Questions?

Adverse drug event call 1-888-296-9067
Dist. By Trifecta Pharmaceuticals USA®
101 NE Third Avenue, Suite 1500
Ft. Lauderdale, FL 33301, USA